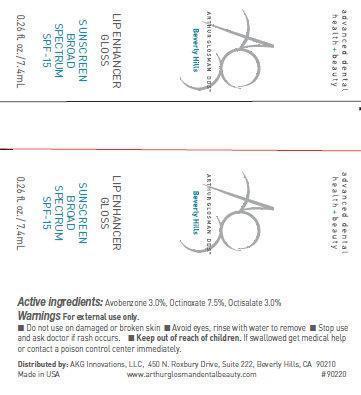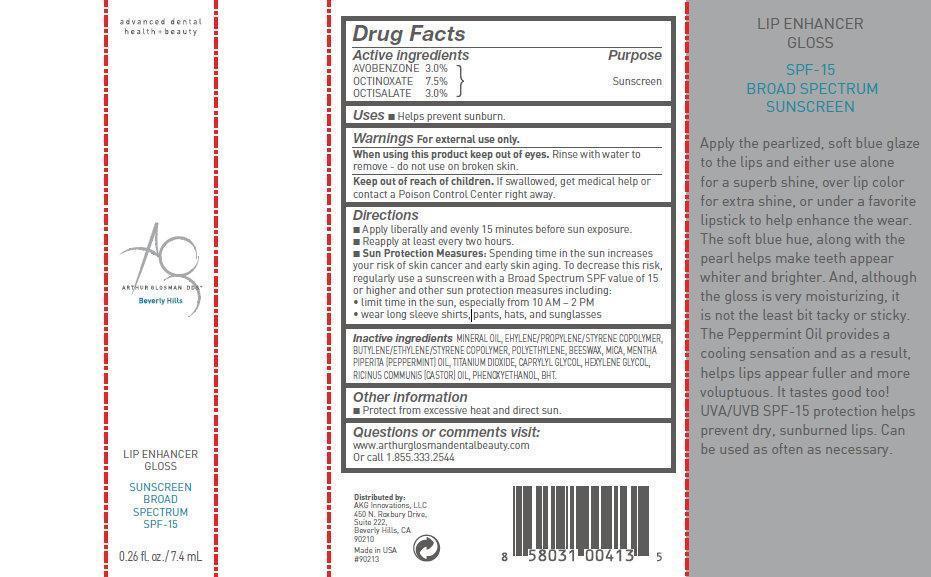 DRUG LABEL: LIP ENHANCER GLOSS SUNSCREEN BROAD SPECTRUM SPF15
NDC: 62111-0210 | Form: GEL
Manufacturer: AKG Innovations LLC
Category: otc | Type: HUMAN OTC DRUG LABEL
Date: 20140213

ACTIVE INGREDIENTS: AVOBENZONE 30 mg/1 mL; OCTINOXATE 75 mg/1 mL; OCTISALATE 30 mg/1 mL
INACTIVE INGREDIENTS: MINERAL OIL; HIGH DENSITY POLYETHYLENE; YELLOW WAX; MICA; MENTHA PIPERITA; TITANIUM DIOXIDE; CAPRYLYL GLYCOL; HEXYLENE GLYCOL; CASTOR OIL; PHENOXYETHANOL; BUTYLATED HYDROXYTOLUENE

LIP ENHANCER GLOSS SUNSCREEN BROAD SPECTRUM SPF15

Active ingredients

AVOBENZONE 3.0%

OCTINOXATE 7.5%

OCTISALATE 3.0%

Purpose

Sunscreen

Uses

Helps prevent sunburn.

Warnings

For external use only

When using this product keep out of eyes.

Rinse with water to remove - do not use on broken skin.

Keep out of reach of children.

If swallowed, get medical help or contact a Poison Control Center right away.

Directions

■Apply liberally and evenly 15 minutes before sun exposure.

■Reapply at least every two hours.

■Sun Protection Measures: Spending time in the sun increases

your risk of skin cancer and early skin aging. To decrease this risk,

regularly use a sunscreen with a Broad Spectrum SPF value of 15

or higher and other sun protection measures including:

• limit time in the sun, especially from 10 AM – 2 PM

• wear long sleeve shirts, pants, hats, and sunglasses

Inactive ingredients

MINERAL OIL, EHYLENE/PROPYLENE/STYRENE COPOLYMER,

BUTYLENE/ETHYLENE/STYRENE COPOLYMER, POLYETHYLENE, BEESWAX, MICA, MENTHA

PIPERITA (PEPPERMINT) OIL, TITANIUM DIOXIDE, CAPRYLYL GLYCOL, HEXYLENE GLYCOL,

RICINUS COMMUNIS (CASTOR) OIL, PHENOXYETHANOL, BHT

Other information

■Protect from excessive heat and direct sun.

Questions or comments visit:

www.arthurglosmandentalbeauty.com

Or call 1.855.333.2544

LIP ENHANCER GLOSS SUNSCREEN BROAD SPECTRUM SPF-15 (62111-0210-1)

advanced dental health - beauty

ARTHUR GLOSMAN DDS

Beverly Hills

LIP ENHANCER

GLOSS

SUNSCREEN

BROAD

SPECTRUM

SPF-15

0.26 fl. oz. / 7.4 mL

Distributed by:

AKG Innovations, LLC

450 N. Roxbury Drive,

Suite 222,

Beverly Hills, CA

90210

Made in USA

#90213

LIP ENHANCER

GLOSS

SPF-15

BROAD SPECTRUM

SUNSCREEN

Apply the pearlized, soft blue glaze

to the lips and either use alone

for a superb shine, over lip color

for extra shine, or under a favorite

lipstick to help enhance the wear.

The soft blue hue, along with the

pearl helps make teeth appear

whiter and brighter. And, although

the gloss is very moisturizing, it

is not the least bit tacky or sticky.

The Peppermint Oil provides a

cooling sensation and as a result,

helps lips appear fuller and more

voluptuous. It tastes good too!

UVA/UVB SPF-15 protection helps

prevent dry, sunburned lips. Can

be used as often as necessary.